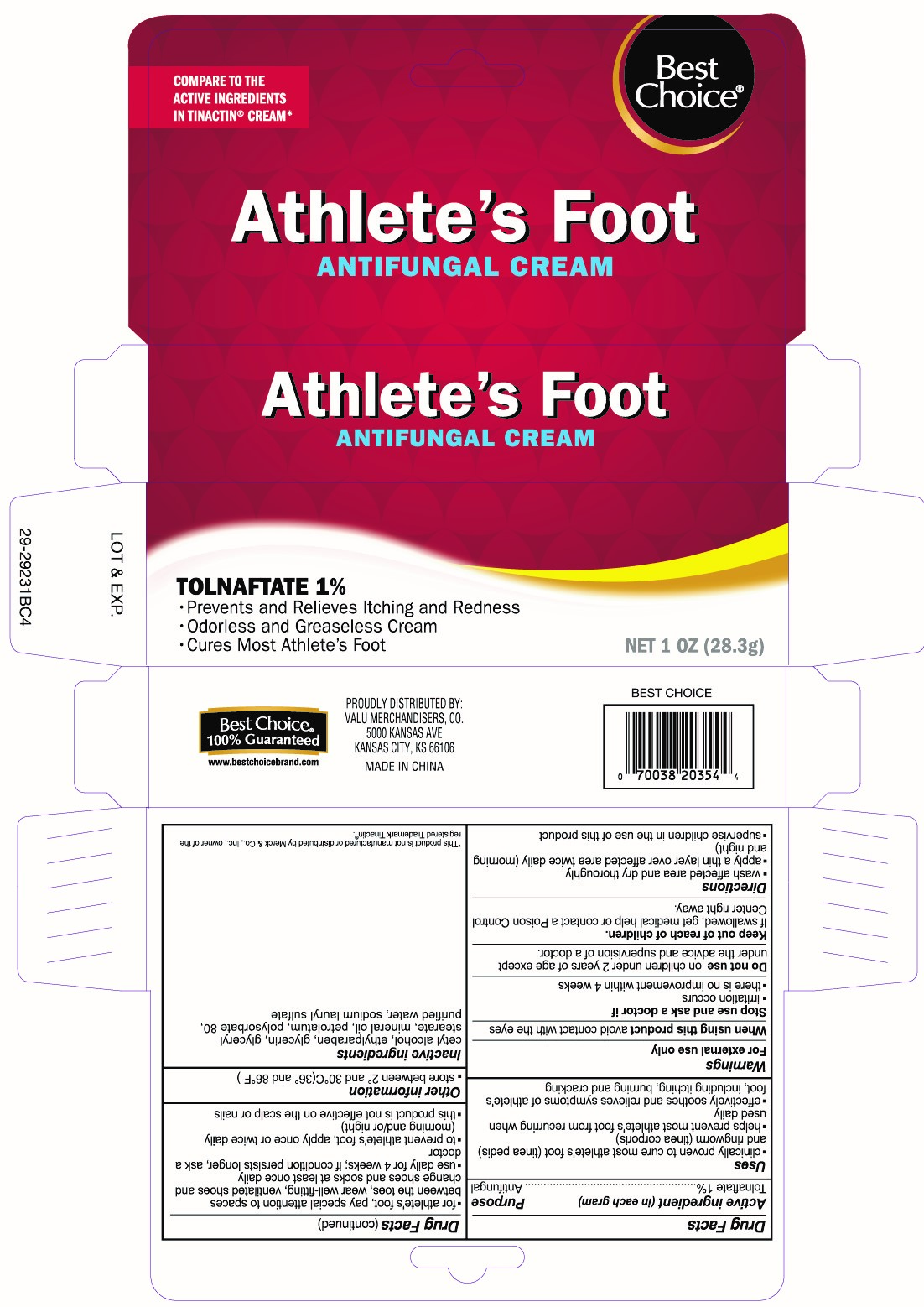 DRUG LABEL: Tolnaftate
NDC: 63941-354 | Form: CREAM
Manufacturer: Valu Merchandisers, Co.
Category: otc | Type: HUMAN OTC DRUG LABEL
Date: 20230208

ACTIVE INGREDIENTS: TOLNAFTATE 1 g/100 g
INACTIVE INGREDIENTS: POLYSORBATE 80; CETYL ALCOHOL; GLYCERYL MONOSTEARATE; PETROLATUM; GLYCERIN; ETHYLPARABEN; MINERAL OIL; WATER; SODIUM LAURYL SULFATE

Best Choice Tolnaftate 1% Cream

Active ingredient (in each gram)

Tolnaftate 1%

Purpose

Antifungal

Uses

- clinically proven to cure most athlete's foot (tinea pedis) and ringworm (tinea corporis)
- helps prevnet most athlete's foot from recurring when used daily
- effectively soothes and relieves symptoms of athlete's foot, including itching, burning and cracking

Warnings

For external use only

When using this product

avoid contact with the eyes

Stop use and ask a doctor if

- irritation occurs
- there is no improvement within 4 weeks

Do not use

on children under 2 years of age except under the advice and supervision of a doctor.

Keep out of reach of children.

If swallowed, get medical help or contact a Poison Control Center right away.

Directions

- for athlete's foot, pay special attention to spaces between the toes, wear well-fitting, ventilated shoes and change shoes and socks at least once daily
- use daily for 4 weeks; if condition persists longer, ask a doctor
- to prevent athlete's foot, apply once or twice daily (morning and/or night)
- this product is not effective on the scalp or nails

Inactive ingredients

cetyl alcohol, ethylparaben, glycerin, glyceryl stearate, mineral oil, petrolatum, polysorbate 80, purified water, sodium lauryl sulfate

Other information

- store between 2 and 30C (36 and 86F)

Package label

Best Choice Tolnaftate 1%